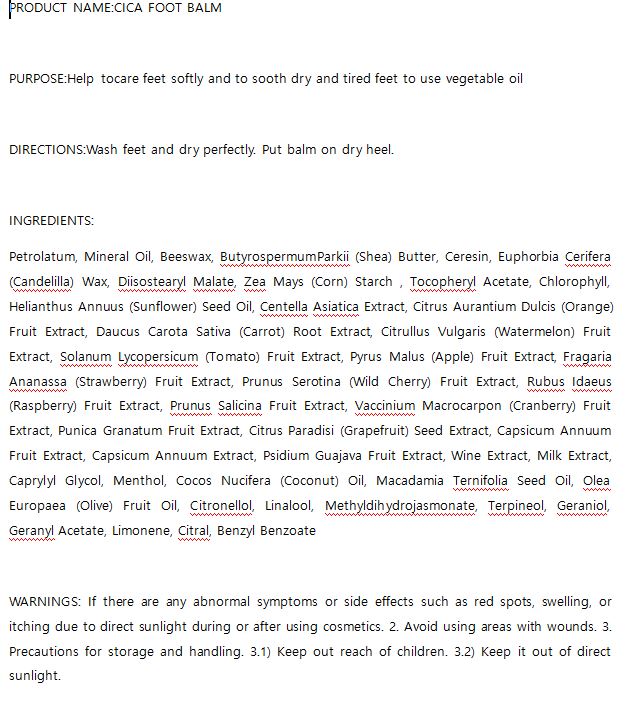 DRUG LABEL: W.SKIN CICA FOOT BALM
NDC: 74997-0017 | Form: STICK
Manufacturer: J&J COMPANY
Category: otc | Type: HUMAN OTC DRUG LABEL
Date: 20210507

ACTIVE INGREDIENTS: PETROLATUM 32.461 g/100 g; YELLOW WAX 15 g/100 g
INACTIVE INGREDIENTS: MENTHOL; CERESIN

J&J COMPANY - STOP-AGING PEPTIDE TONER

ACTIVE INGREDIENT

Petrolatum 32.461

Beeswax 15

INACTIVE INGREDIENT

Petrolatum, Mineral Oil, Beeswax, ButyrospermumParkii (Shea) Butter, Ceresin, Euphorbia Cerifera (Candelilla) Wax, Diisostearyl Malate, Zea Mays (Corn) Starch , Tocopheryl Acetate, Chlorophyll, Helianthus Annuus (Sunflower) Seed Oil, Centella Asiatica Extract, Citrus Aurantium Dulcis (Orange) Fruit Extract, Daucus Carota Sativa (Carrot) Root Extract, Citrullus Vulgaris (Watermelon) Fruit Extract, Solanum Lycopersicum (Tomato) Fruit Extract, Pyrus Malus (Apple) Fruit Extract, Fragaria Ananassa (Strawberry) Fruit Extract, Prunus Serotina (Wild Cherry) Fruit Extract, Rubus Idaeus (Raspberry) Fruit Extract, Prunus Salicina Fruit Extract, Vaccinium Macrocarpon (Cranberry) Fruit Extract, Punica Granatum Fruit Extract, Citrus Paradisi (Grapefruit) Seed Extract, Capsicum Annuum Fruit Extract, Capsicum Annuum Extract, Psidium Guajava Fruit Extract, Wine Extract, Milk Extract, Caprylyl Glycol, Menthol, Cocos Nucifera (Coconut) Oil, Macadamia Ternifolia Seed Oil, Olea Europaea (Olive) Fruit Oil, Citronellol, Linalool, Methyldihydrojasmonate, Terpineol, Geraniol, Geranyl Acetate, Limonene, Citral, Benzyl Benzoate

PURPOSE

Help tocare feet softly and to sooth dry and tired feet to use vegetable oil

keep out of reach of the children

INDICATIONS AND USAGE

Wash feet and dry perfectly. Put balm on dry heel.

WARNINGS

If there are any abnormal symptoms or side effects such as red spots, swelling, or itching due to direct sunlight during or after using cosmetics. 2. Avoid using areas with wounds. 3. Precautions for storage and handling. 3.1) Keep out reach of children. 3.2) Keep it out of direct sunlight.

DOSAGE AND ADMINISTRATION

for external use only